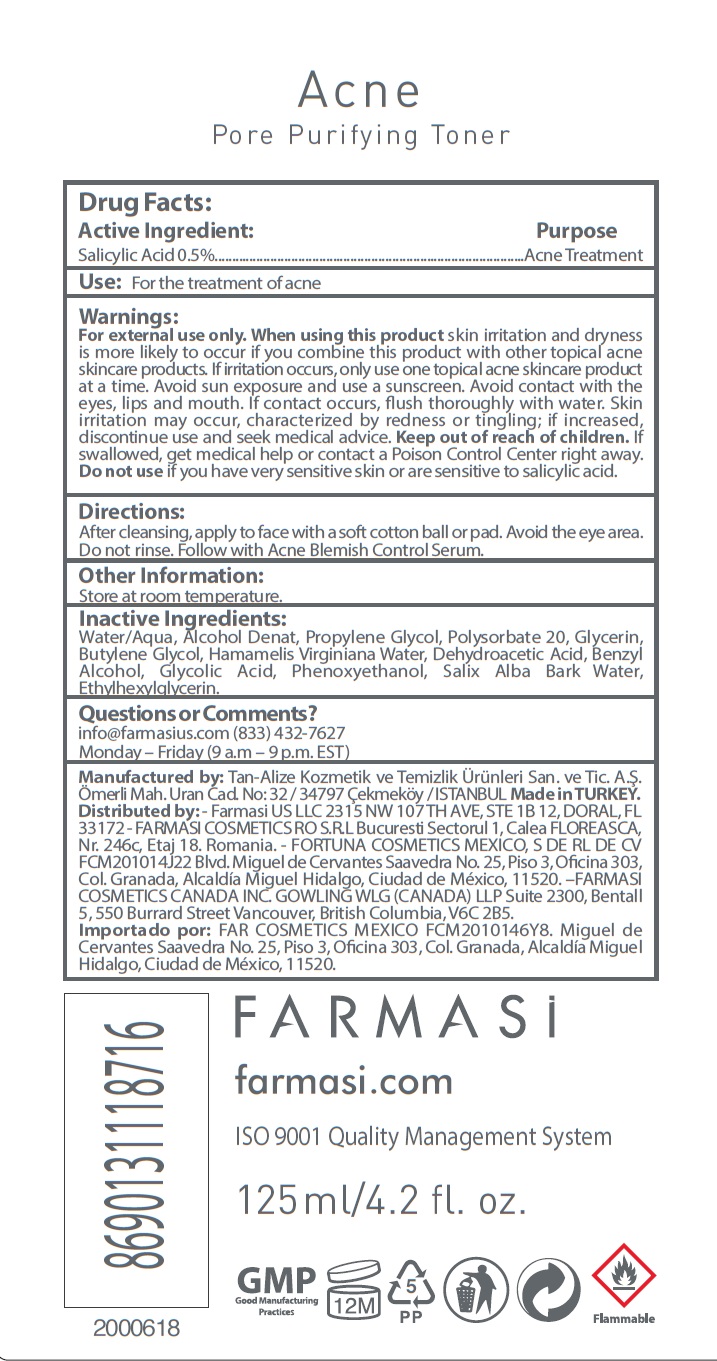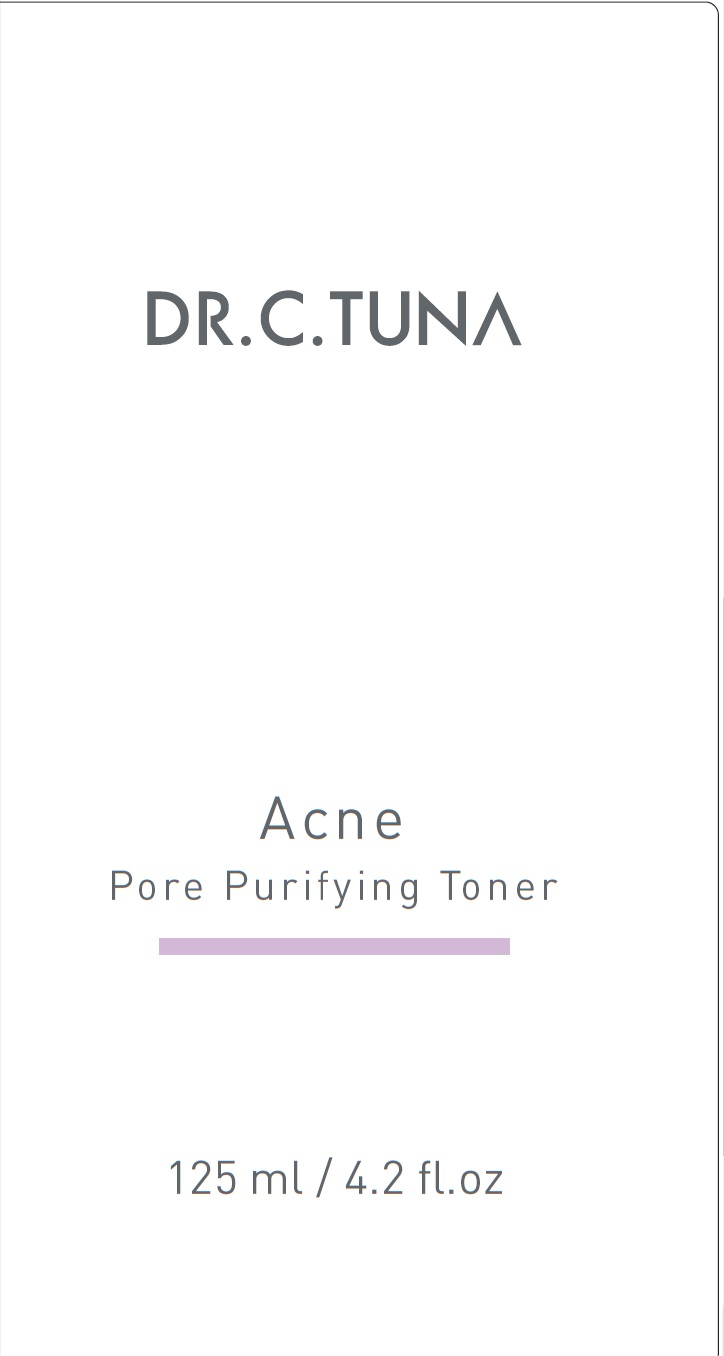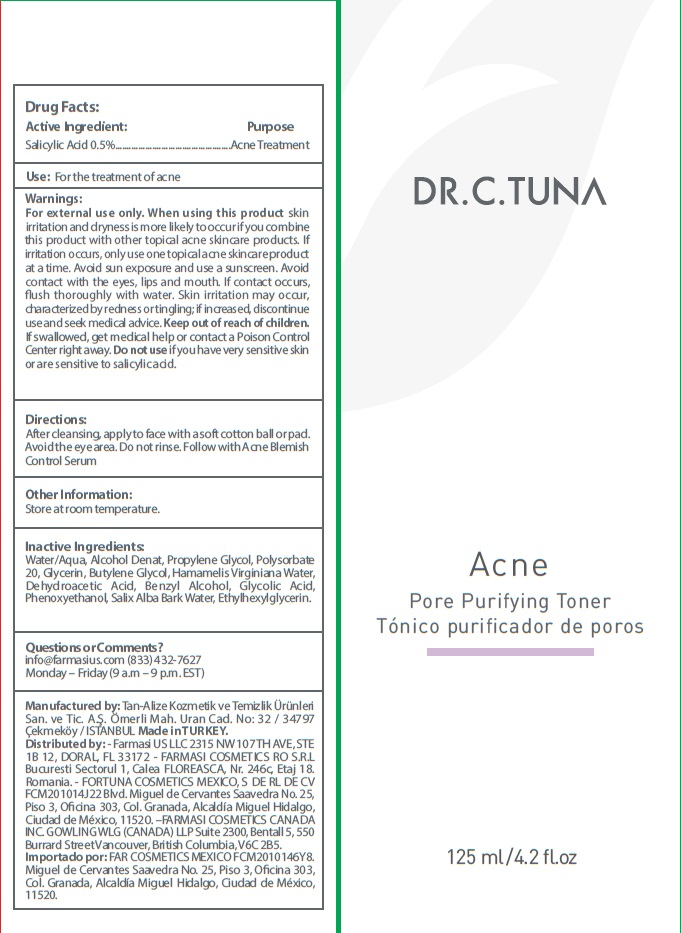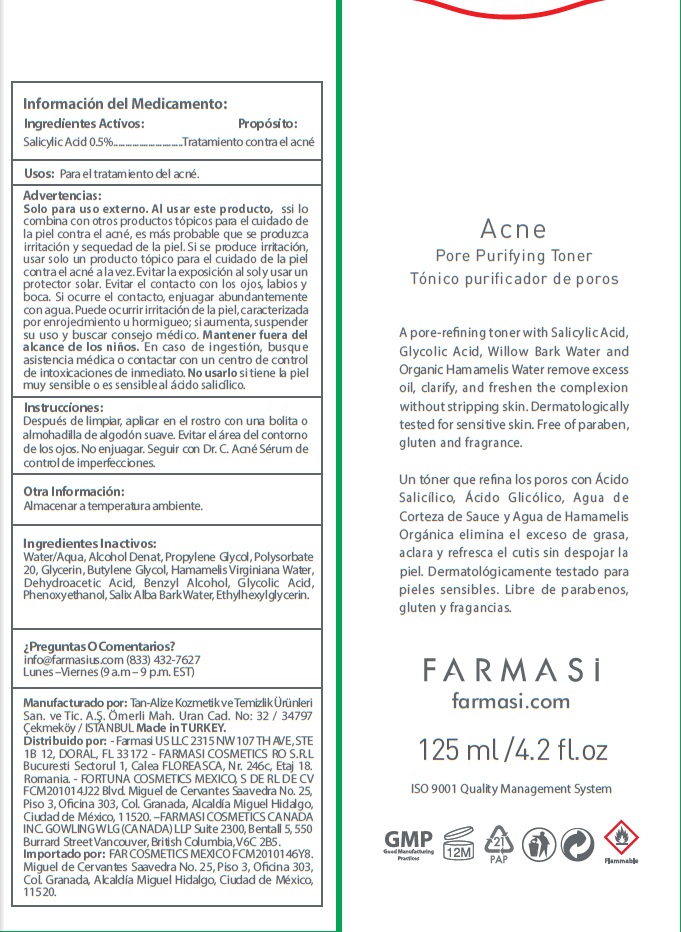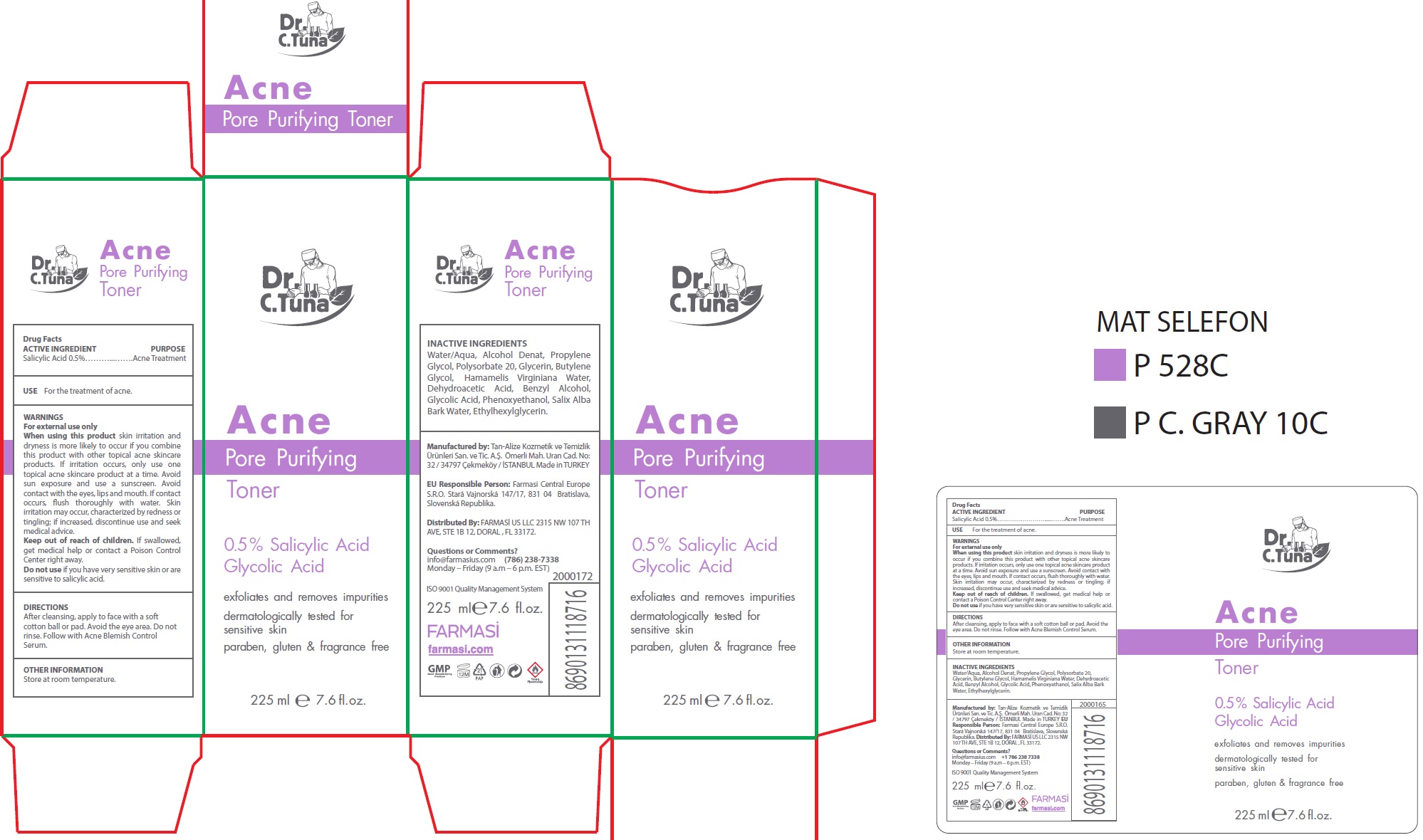 DRUG LABEL: Dr. C. Tuna Acne Pore Purifying Toner
NDC: 74690-009 | Form: LIQUID
Manufacturer: Farmasi US LLC
Category: otc | Type: HUMAN OTC DRUG LABEL
Date: 20231105

ACTIVE INGREDIENTS: SALICYLIC ACID 5 mg/1 mL
INACTIVE INGREDIENTS: WATER; ALCOHOL; PROPYLENE GLYCOL; POLYSORBATE 20; GLYCERIN; BUTYLENE GLYCOL; HAMAMELIS VIRGINIANA ROOT BARK/STEM BARK; DEHYDROACETIC ACID; BENZYL ALCOHOL; GLYCOLIC ACID; PHENOXYETHANOL; SALIX ALBA BARK VOLATILE OIL; ETHYLHEXYLGLYCERIN

Dr. C. Tuna Acne Pore Purifying Toner

ACTIVE INGREDIENT

Salicylic Acid 0.5%

PURPOSE

Acne Treatment

USE

For the treatment of acne.

WARNINGS

For external use only

When using this product

skin irritation and dryness is more likely to occur if you combine this product with other topical acne skincare products. If irritation occurs, only use one topical acne skincare product at a time. Avoid sun exposure and use a sunscreen. Avoid contact with the eyes, lips and mouth. If contact occurs, flush thoroughly with water. Skin irritation may occur, characterized by redness or tingling; if increased, discontinue use and seek medical advice.

Keep out of reach of children.

If swallowed, get medical help or contact a Poison Control Center right away.

Do not use

if you have very sensitive skin or are sensitive to salicylic acid.

DIRECTIONS

After cleansing, apply to face with a soft cotton ball or pad. Avoid the eye area. Do not rinse. Follow with Acne Blemish Control Serum.

OTHER INFORMATION

Store at room temperature.

INACTIVE INGREDIENTS

Water/Aqua, Alcohol Denat, Propylene Glycol, Polysorbate 20, Glycerin, Butylene Glycol, Hamamelis Virginiana Water, Dehydroacetic Acid, Benzyl Alcohol, Glycolic Acid, Phenoxyethanol, Salix Alba Bark Water, Ethylhexylglycerin.

Questions or Comments?

info@farmasius.com Monday – Friday (9 a.m – 6 p.m. EST) (786) 238-7338